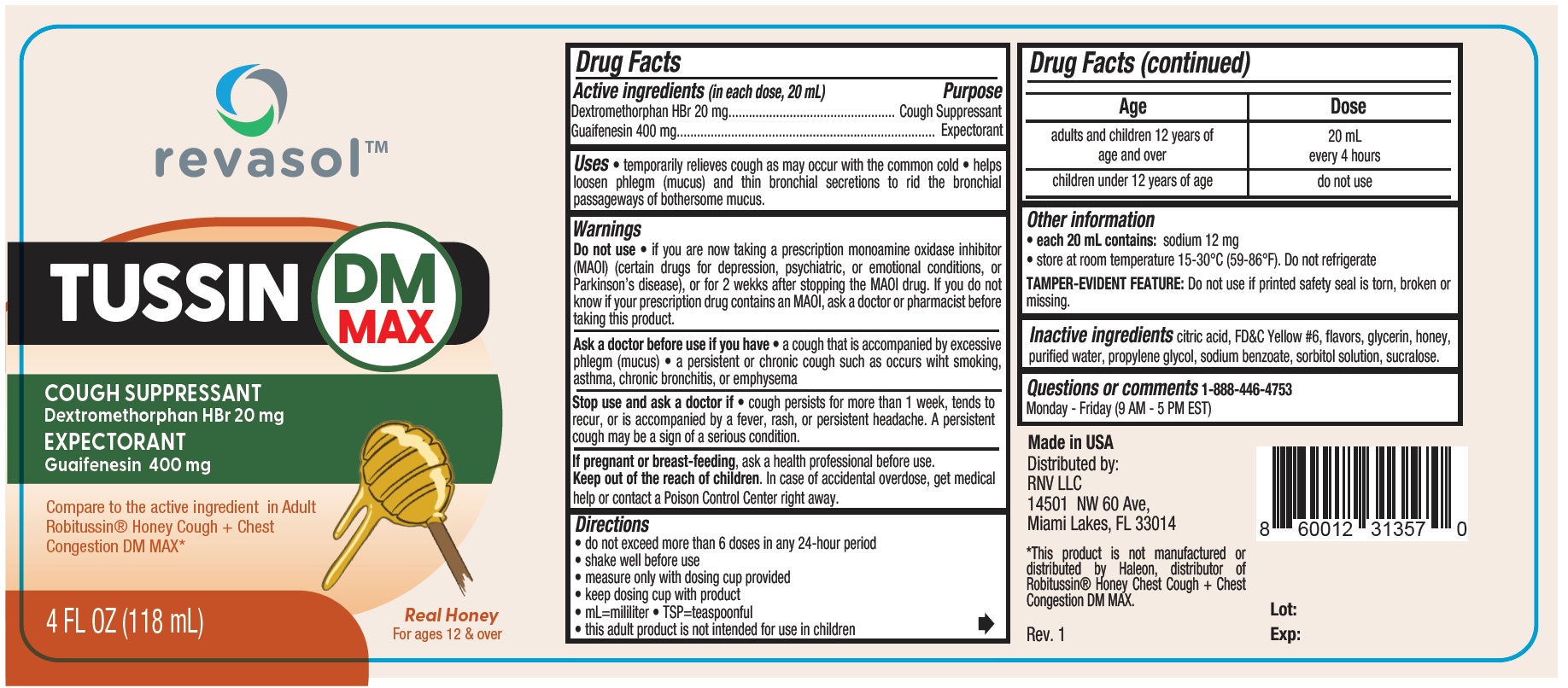 DRUG LABEL: Revasol Tussin DM Max with Honey
NDC: 84379-274 | Form: LIQUID
Manufacturer: Rnv LLC
Category: otc | Type: HUMAN OTC DRUG LABEL
Date: 20250321

ACTIVE INGREDIENTS: GUAIFENESIN 400 mg/20 mL; DEXTROMETHORPHAN HYDROBROMIDE 20 mg/20 mL
INACTIVE INGREDIENTS: HONEY; FD&C YELLOW NO. 6; WATER; GLYCERIN; ANHYDROUS CITRIC ACID; SUCRALOSE; SORBITOL SOLUTION; XANTHAN GUM; SODIUM BENZOATE; PROPYLENE GLYCOL

Revasol Tussin DM Max with Honey

Active ingredients (in each dose, 20 mL) Purpose

Dextromethorphan HBr 20 mg..........................Cough Suppressant

Guaifenesin 400 mg..........................................Expectorant

PURPOSE

Cough Suppressant

Expectorant

Uses

• temporarily relieves cough as may occur with the common cold • helps
loosen phlegm (mucus) and thin bronchial secretions to rid the bronchial
passageways of bothersome mucus.

Warnings

Do not use • if you are now taking a prescription monoamine oxidase inhibitor
(MAOI) (certain drugs for depression, psychiatric, or emotional conditions, or
Parkinson’s disease), or for 2 wekks after stopping the MAOI drug. If you do not
know if your prescription drug contains an MAOI, ask a doctor or pharmacist before
taking this product.

Ask a doctor before use if you have

• a cough that is accompanied by excessive
phlegm (mucus) • a persistent or chronic cough such as occurs wiht smoking,
asthma, chronic bronchitis, or emphysema

Stop use and ask a doctor if

• cough persists for more than 1 week, tends to
recur, or is accompanied by a fever, rash, or persistent headache. A persistent
cough may be a sign of a serious condition.

PREGNANCY OR BREAST FEEDING

If pregnant or breast-feeding, ask a health professional before use.

KEEP OUT OF REACH OF CHILDREN

Keep out of the reach of children. In case of accidental overdose, get medical
help or contact a Poison Control Center right away.

Directions
• do not exceed more than 6 doses in any 24-hour period
• shake well before use
• measure only with dosing cup provided
• keep dosing cup with product
• mL=mililiter • TSP=teaspoonful
• this adult product is not intended for use in children

Age | Dose
adults and children 12 years of age and over | 20 mL every 4 hours
children under 12 years of age | do not use

Other information
• each 20 mL contains: sodium 12 mg
• store at room temperature 15-30°C (59-86°F). Do not refrigerate

TAMPER-EVIDENT FEATURE: Do not use if printed safety seal is torn, broken or missing.

Inactive ingredients

citric acid, FD&C Yellow #6, flavors, glycerin, honey,
purified water, propylene glycol, sodium benzoate, sorbitol solution, sucralose.

Questions or comments 1-888-446-4753
Monday - Friday (9 AM - 5 PM EST)